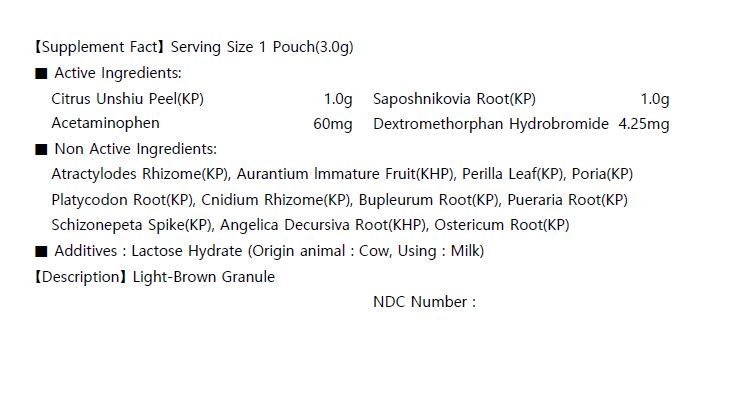 DRUG LABEL: PEDOXAN Extract
NDC: 73442-0014 | Form: GRANULE
Manufacturer: I World Pharmaceutical Co., Ltd.
Category: otc | Type: HUMAN OTC DRUG LABEL
Date: 20200916

ACTIVE INGREDIENTS: TANGERINE 1 g/3 g; ACETAMINOPHEN 0.06 g/3 g; SAPOSHNIKOVIA DIVARICATA ROOT 1 g/3 g; DEXTROMETHORPHAN HYDROBROMIDE 0.00425 g/3 g
INACTIVE INGREDIENTS: LACTOSE MONOHYDRATE

ACTIVE INGREDIENT

Citrus Unshiu Peel(KP)

Saposhnikovia Root(KP)

Acetaminophen

Dextromethorphan Hydrobromide

PURPOSE

minor aches and pain from colds, headache fever

Keep out of reach of children

INDICATIONS AND USAGE

for adults take 1 pouch per intake, 3 times a day, before or between meals

Keep out of reach of children. In case of overdose, get medical help or contact a Poison Control Center right away.

INACTIVE INGREDIENT

Atractylodes Rhizome(KP), Aurantium lmmature Fruit(KHP), Perilla Leaf(KP), Poria(KP)

Platycodon Root(KP), Cnidium Rhizome(KP), Bupleurum Root(KP), Pueraria Root(KP)

Schizonepeta Spike(KP), Angelica Decursiva Root(KHP), Ostericum Root(KP)

DOSAGE AND ADMINISTRATION

For oral use only